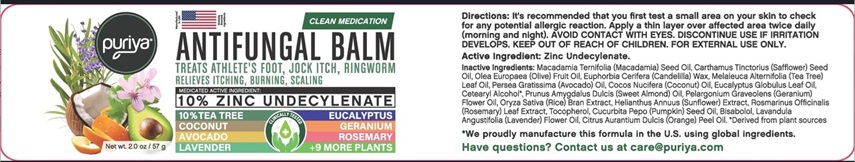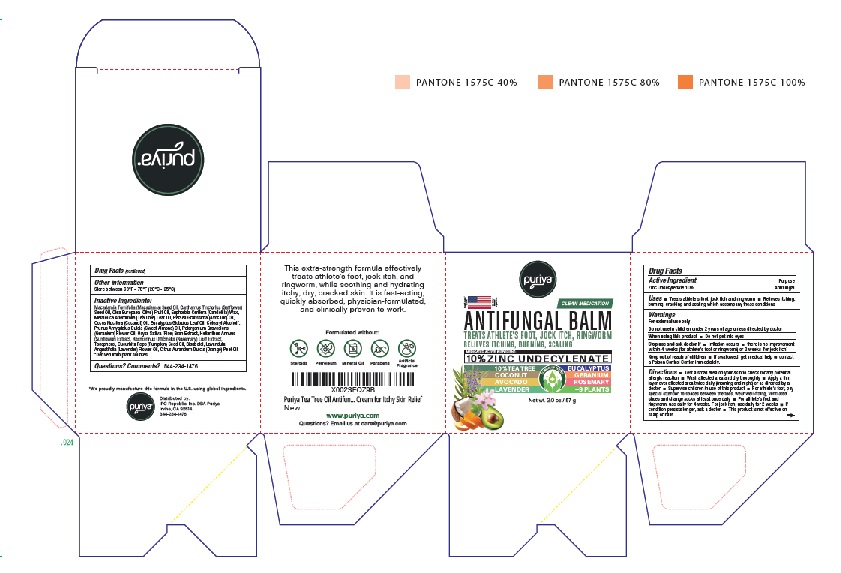 DRUG LABEL: Puriya Antifungal Balm
NDC: 84711-001 | Form: CREAM
Manufacturer: IPC Republic, Inc.
Category: otc | Type: HUMAN OTC DRUG LABEL
Date: 20260122

ACTIVE INGREDIENTS: ZINC UNDECYLENATE 5.7 g/57 g
INACTIVE INGREDIENTS: MACADAMIA OIL; SAFFLOWER OIL; OLIVE OIL; CANDELILLA WAX; TEA TREE OIL; AVOCADO OIL; COCONUT OIL; EUCALYPTUS OIL; CETOSTEARYL ALCOHOL; ALMOND OIL; PELARGONIUM GRAVEOLENS FLOWER OIL; RICE BRAN; SUNFLOWER OIL; ROSEMARY; TOCOPHEROL; PUMPKIN SEED OIL; LEVOMENOL; LAVENDER OIL; ORANGE OIL

Puriya Antifungal Balm

DRUG FACTS

Active Ingredient
Zinc Undecylenate 10%

Purpose

Antifungal

INDICATIONS AND USAGE

Uses• Treats athlete's loot, jock itch and ringworm • Relieves itchlng,
burning, cracking and scaling which accompany these conditions

Warnings

For external use only

DO NOT USE

Do oot use In children under 2 years of age unless directed by doctor

When using this product • Do not get into eyes

Stop use and ask doctor if • Irritation occurs • there is no improvement
within 4 weeks (for athlete's foot or ringworm) or 2 weeks (for jock Itch)

Keep out of reach of children • If swallowed, get medical help or call a Poison Control Center immediately.

DOSAGE AND ADMINISTRATION

Directions • Test asmall area on your skin to check for any potential
allergic reaction • Wash affected area and dry thoroughly • Apply a thin
layer over affected area twice dally (morning and night) or as directed by a
doctor • Supervise children in use of this product • For athlete's foot, pay
special attention to spaces between the toes, wear well-fitting, ventilated
shoes and change socks at least once dally • For athlete's foot and
ringworm, use dally for 4 weeks. For jock itch, use dally for 2 weeks • If
condition persists longer, ask a doctor • This product is not effective on
scalp or nails.

Other infonnation
Store between 68°F - 78°F (20°C - 25°C)

Inactive Ingredients:
Macadamia Temifolia (Macadamia) Seed Oil, Carthamus Tinctorius (Safflower)
Seed Oil, Olea Europaea (Olive) Fruit Oil, Euphorbia Cerifera (Candelilla) Wax,
Melaleuca Altemifolia (Tea Tree) Leaf Oil, Persea Gratissima (Avocado) Oil,
Cocos Nucifera (Coconut) Oil, Eucalyptus Globulus Leaf Oil, Cetearyl Alcohol*,
Prunus Amygdalus Dulcis (Sweet Almond) Oil, Pelargonium Graveolens
(Geranium) Flower Oil, Oryza Sativa (Rice) Bran Extract, Helianthus Annuus
(Sunflower) Extract, Rosmarinus Officinalis (Rosemary) Leaf Extract,
Tocopherol, Cucurbita Pepo (Pumpkin) Seed Oil, Bisabolol, Lavandula
Angustifolia (Lavender) Flower Oil, Citrus Aurantium Dulcis (Orange) Peel Oil.
*Derived from plant sources

Questions? Comments? 844-234-1476

Product Labeling

puriya®

ANTIFUNGAL BALM

Treats Athlete's Foot | Jock Itch | Ringworm
Physician Formulated |16 Powerful Botanicals

Zinc Undecylenate Net wt 2.0 oz / 57 g

Distributed by:
IPC Republic, Inc. DBA Puriya
Los Angeles, CA 90013
844-234-1476

www.puriya.com
Questions? Email usatservice@Puriya.com

Box

Jar

res